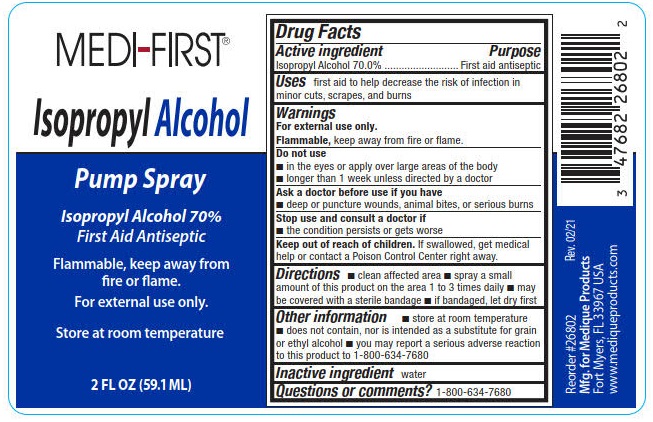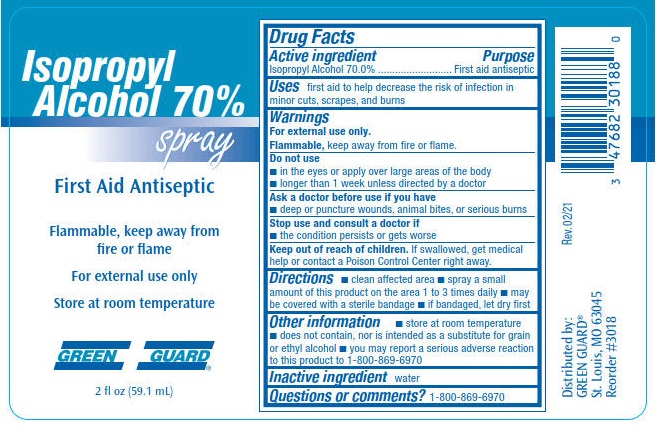 DRUG LABEL: Medi-First Isopropyl Alcohol 70%
NDC: 47682-264 | Form: SPRAY
Manufacturer: Unifirst First Aid Corporation
Category: otc | Type: HUMAN OTC DRUG LABEL
Date: 20240117

ACTIVE INGREDIENTS: ISOPROPYL ALCOHOL 70 mL/100 mL
INACTIVE INGREDIENTS: WATER

Isopropyl Alcohol 70% Spray

Drug Facts

Active ingredient

Isopropyl Alcohol 70.0%

Purpose

First aid antiseptic

Uses

first aid to help prevent infection in minor cuts, scrapes, and burns

Warnings

For external use only.

Flammable, keep away from fire or flame.

Do not use

- in the eyes or apply over large areas of the body
- londer than 1 week unless directed by a doctor

Ask a doctor before use if you have

- deep or puncture wounds, animal bites, or serious burns

Stop use and consult a doctor if

- the condition persists or gets worse

Keep out of reach of children.

If swallowed, get medical help or contact a Poison Control Center right away.

Directions

- clean affected area
- spray a small amount of this product on the area 1 to 3 times daily
- may be covered with a sterile bandage
- if bandaged, let dry first

Other information

- store at room temperature
- does not contain, nor is intended as a substitute for grain or ethyl alcohol
- you may report a serious adverse reaction to this product to 1-800-869-6970

Inactive ingredient water

Questions or comments? 1-800-869-6970

PACKAGE LABEL

Green guard

Isopropyl Alcohol 70% spray

First Aid Antiseptic

Flammable, keep away from fire or flame

For external use only

Store at room temperature

2 fl oz (59.1 mL)

PACKAGE LABEL

Medi-First®

Isopropyl Alcohol

Pump Spray

Isopropyl Alcohol 70%

First Aid Antiseptic

Flammable, keep away from fire or flame.

For external use only.

Store at room temperature

2 FL OZ (59.1 ML)